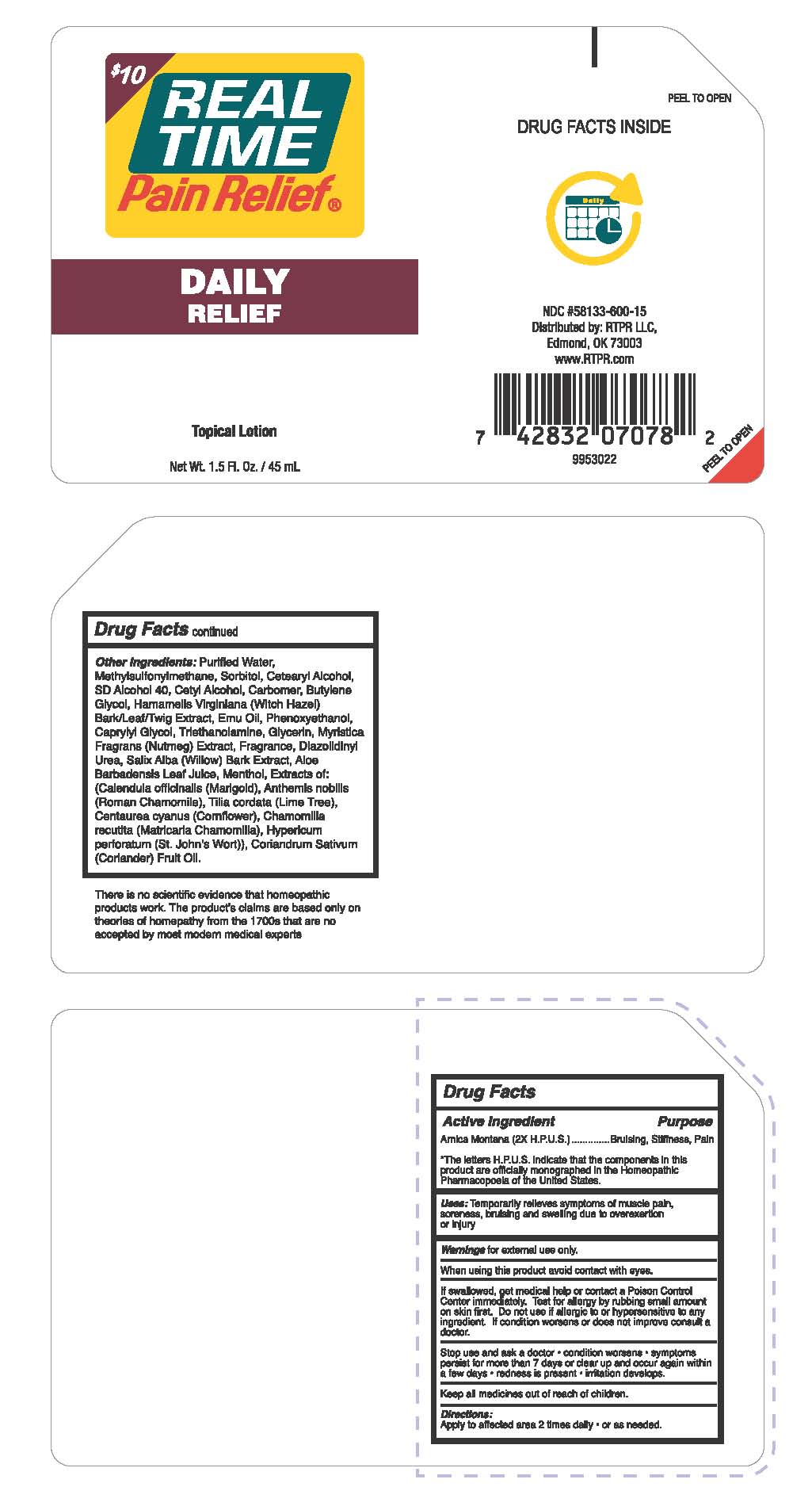 DRUG LABEL: Real Time Pain Relief Daily Relief
NDC: 58133-300 | Form: LOTION
Manufacturer: Cosmetic Specialty Labs, Inc.
Category: homeopathic | Type: HUMAN OTC DRUG LABEL
Date: 20180103

ACTIVE INGREDIENTS: ARNICA MONTANA 2 mg/100 mL
INACTIVE INGREDIENTS: EMU OIL; PHENOXYETHANOL; GLYCERIN; MYRISTICA FRAGRANS FRUIT; TILIA CORDATA FLOWER; CENTAUREA CYANUS FLOWER; MATRICARIA CHAMOMILLA; CORIANDRUM SATIVUM WHOLE; DIMETHYL SULFONE; SORBITOL; SALIX ALBA BARK; CETYL ALCOHOL; WATER; CETOSTEARYL ALCOHOL; CARBOMER 934; BUTYLENE GLYCOL; CAPRYLYL GLYCOL; DIAZOLIDINYL UREA; ALOE; MENTHOL; CALENDULA OFFICINALIS SEED OIL; CHAMOMILE FLOWER OIL; HYPERICUM PERFORATUM; 2,2-DICHLORO-1-(2-CHLOROPHENYL)ETHANOL; HAMAMELIS VIRGINIANA LEAF; CLOPYRALID TRIETHANOLAMINE

Real Time Pain Relief Daily Relief

Active Ingredient

Arnica Montana (2X H.P.U.S.)

*The letters H.P.U.S. indicate that the components in this product are officially monographed in the Homeopathic Pharmacopoeia of the United States.

Purpose

Bruising, Stiffness, Pain

Uses:

Temporarily relieves symptoms of muscle pain, soreness, bruising and swelling due to overexertion or injury.

Warnings

for external use only

When using this product

avoid contact with eyes

Warnings and Precautions

If swallowed, get medical help or contact a Poison Control Center immediately. Test for allergy by rubbing small amount on skin first. Do not use if allergic to or hypersensitive to any ingredient. If condition worsens or does not improve consult a doctor.

Stop use and ask a doctor

- condition worsens
- symptoms persist for more than 7 days or clear up and occur again within a few days
- redness is present
- irritation develops

Keep all medicines out of reach of children.

Directions

Apply to affected area 2 times daily

- or a needed.

Other Ingredients

Purified Water, Methylsulfonylmethane, Sorbitol, Cetearyl Alcohol, SD Alcohol40, Cetyl Alcohol, Carbomer, Butylene Glycol, Hamamelis Virginiana (Witch Hazel) Bark/Leaf/Twig Extract, Emu Oil, Phenoxyethanol, Caprylyl Glycol, Triethanolamine, Gycerin, Myristica Fragrans (Nutmeg) Extract, Fragrance, Diazolidinyl Urea, Salix Alba (Willow) Bark Extract, Aloe Barbadensis Leaf Juice, Menthol, Extracts of: (Calendula officianlis (Marigold), Anthemis nobilis (Roman Chamomile), Tilia cordata (Lime Tree), Centaurea cyanus (Cornflower), Chamomilla recutita (Matricaria Chamomilla), Hypericum perforatum (St. John’s Wort)), Coriandrum Sativum (Coriander) Fruit Oil.